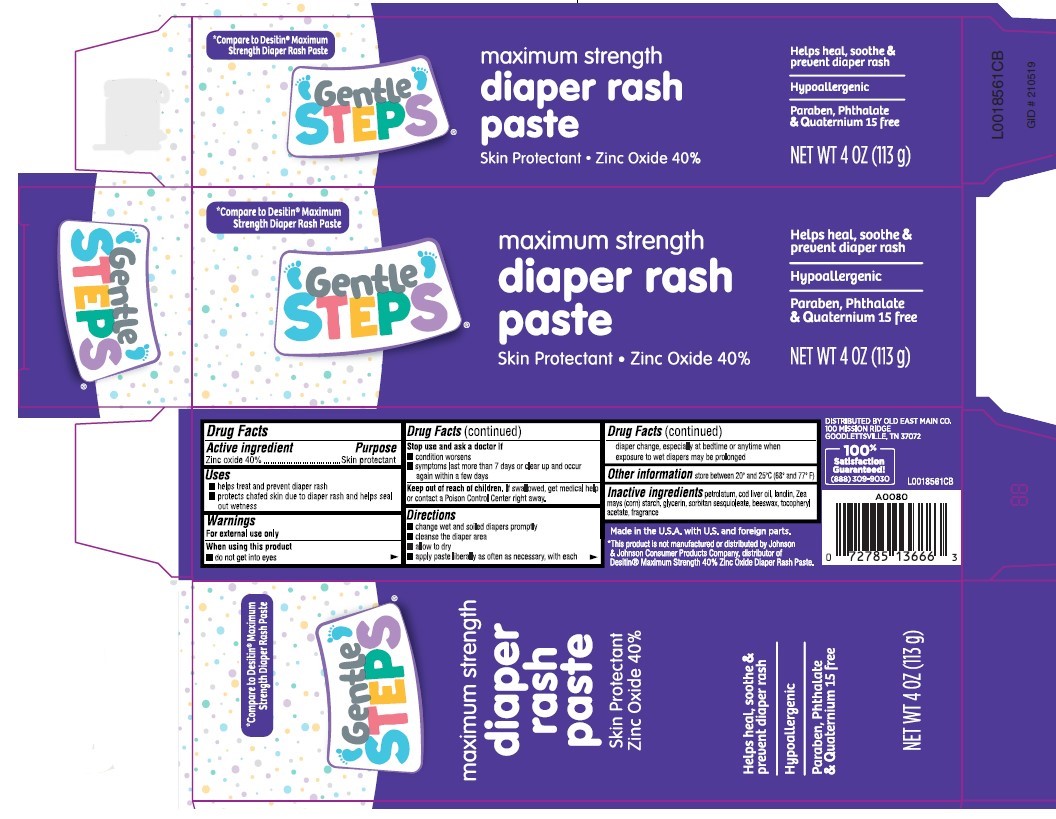 DRUG LABEL: Diaper Rash
NDC: 55910-020 | Form: PASTE
Manufacturer: Old East Main Co.
Category: otc | Type: HUMAN OTC DRUG LABEL
Date: 20260302

ACTIVE INGREDIENTS: ZINC OXIDE 400 mg/1 g
INACTIVE INGREDIENTS: PETROLATUM; COD LIVER OIL; LANOLIN; STARCH, CORN; GLYCERIN; SORBITAN SESQUIOLEATE; YELLOW WAX; .ALPHA.-TOCOPHEROL ACETATE

Gentle Steps 020.002/020AC-AD
Diaper Rash Ointment 40% Zinc Oxide

Active ingredient

Zinc oxide 40%

Purpose

Skin protectant

Uses

- helps treat and prevent diaper rash
- protects chafed skin due to diaper rash and helps seal out wetness

Warnings

For external use only

When using this product

- do not get into eyes

Stop use and ask a doctor if

- condition worsens
- symptoms last more than 7 days or clear up and occur again within a few days

Keep out of reach of children.

If swallowed, get medical help or contact a Poison Control Center right away.

Directions

- change wet and soiled diapers promptly
- cleanse the diaper area
- allow to dry
- apply paste liberally as often as necessary, with each diaper change, especially at bedtime or anytime when exposure to wet diapers may be prolonged

Other information

store between 20⁰ and 25⁰C (68⁰ and 77⁰F)

Inactive ingredients

petrolatum, cod liver oil, lanolin, Zea mays (corn) starch, glycerin, sorbitan sesquioleate, beeswax, tocopheryl acetate, fragrance

Disclaimer

Made in the U.S.A. with U.S. an foreign parts.

*This product is not manufactured or distributed by Johnson & Johnson Consumer Products Company, distributor of DesitinMaximum Strength 40% Zince Oxide Diaper Rash Paste.

Adverse reaction

DISTRIBUTED BY OLD EAST MAIN CO.

100 MISSION RIDGE

GOODLETTSVILLE, TN 37072

100% Quality Guaranteed!

(888)309-9030

Principal display panel

*Compare to Desitin®Maximum Strength Diaper Rash Paste

Gentle STEPS®

maximum strength

diaper rash paste

Skin Protectant • Zinc Oxide 40%

Helps heal, soothe & prevent diaper rash

Hypoallergenic

Paraben, Phthalate & Quaternium 15 free

NET WT 4 OZ (113 g)